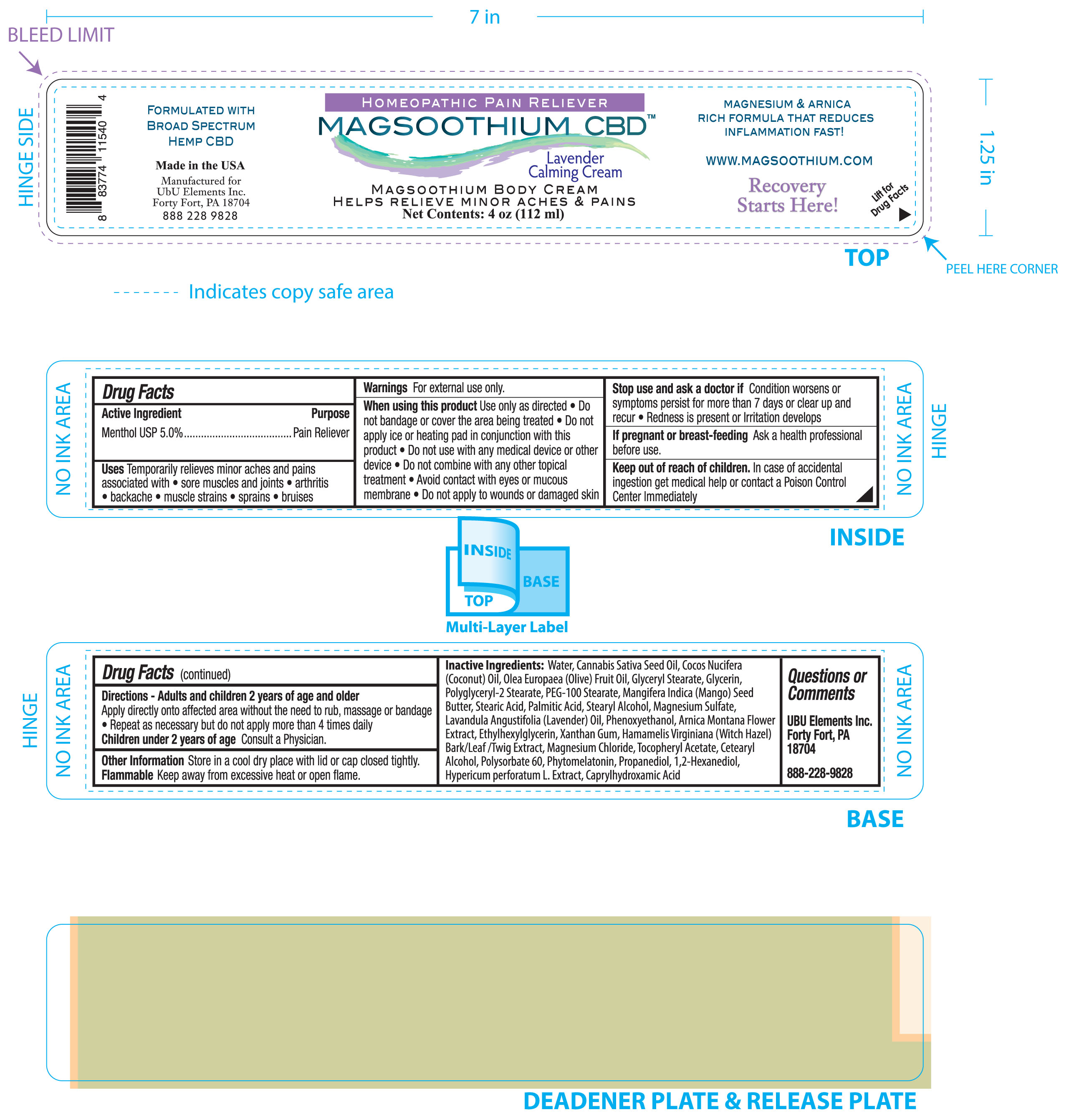 DRUG LABEL: Magsoothium CBD Body Lavender
NDC: 83262-003 | Form: CREAM
Manufacturer: Ubu/Elements, Inc.
Category: otc | Type: HUMAN OTC DRUG LABEL
Date: 20251216

ACTIVE INGREDIENTS: MENTHOL 5 g/100 mL
INACTIVE INGREDIENTS: COCONUT OIL; GLYCERYL MONOSTEARATE; POLYGLYCERYL-2 STEARATE; STEARYL ALCOHOL; MAGNESIUM SULFATE, UNSPECIFIED FORM; PHENOXYETHANOL; .ALPHA.-TOCOPHEROL ACETATE; POLYSORBATE 60; HYPERICUM PERFORATUM WHOLE; ARNICA MONTANA FLOWER; MAGNESIUM CHLORIDE; WATER; CANNABIS SATIVA SEED OIL; STEARIC ACID; PALMITIC ACID; PEG-100 STEARATE; MANGIFERA INDICA SEED BUTTER; LAVENDER OIL; XANTHAN GUM; HAMAMELIS VIRGINIANA TOP; CETOSTEARYL ALCOHOL; 1,2-HEXANEDIOL; OLIVE OIL; PROPANEDIOL; CAPRYLHYDROXAMIC ACID; ETHYLHEXYLGLYCERIN; GLYCERIN

Magsoothium CBD Body Cream Lavender

Active ingredient

Menthol USP 5.0

Purpose

Pain Reliever

PURPOSE

Uses Temporarily relieves minor aches and pains associated with

- sore muscles and joins
- arthritis
- backache
- muscle strans
- sprains
- bruises

Keep out of reach of children. In case of accidental ingestion get medical help or contact a Poison Control Center Immediately

Stop use and ask a doctor if Condition worsens or symptoms persist for more than 7 days or clear up and recur

- Redness is present or irritation

Warnings for external use only.

when using this product Use only as directed

- Do not bandage or cover the area being treated
- Do not apply ice or heating pad in conjunction with this product
- Do not use with any medical device or other device
- Do not combine with any other toipcal treatment
- Avoid contact with eyes or mucous membrane
- Do not apply to wounds or damaged skin

If pregnant or breast-feeding Ask a health professional before use.

DOSAGE AND ADMINISTRATION

Directions - Adults and children 2 years of age and older

Apply directly onto affected area without the need to rub, massage or bandage

- Repeat as necessary, but do not apply more than 4 times daily

Children under 2 years of age Consult a physician

INACTIVE INGREDIENT

Inactive Ingredients: Water, Cannabis Sativa Seed Oil,Cocos Nucifera (Coconut) Oil, Olea Europaea (Olive) Fruit Oil, Glyceryl Stearate, Glycerin, Polyglyceryl-2 Stearate, PEG-100 Stearate, Mangifera Indica (Mango) Seed Butter, Stearic Acid, Palmitic Acid, Stearyl Alcohol, Magnesium Sulfate, Lavandula Angustifolia (Lavender) Oil, Phenoxyethanol, Arnica Montana Flower Extract, Ethylhexylglycerin, Xanthan Gum, Hamamelis Virginiana (Witch Hazel) Bark/Leaf/Twig Extract, Magnesium Chloride, Tocopheryl Acetate, Cetearyl Alcohol, Polysorbate 60, Phytomelatonin, Propanediol, 1,2-Hexanediol, Hypericum Perforatum L. Extract, Caprylhydroxamic Acid.

PACKAGE LABEL

Homeopathic Pain Reliever

Magsoothium CBD

Lavender Calming Cream

Magsoothium Body Cream

Helps relieve minor aches & pains

Net Contents: 4 oz (112 ml)